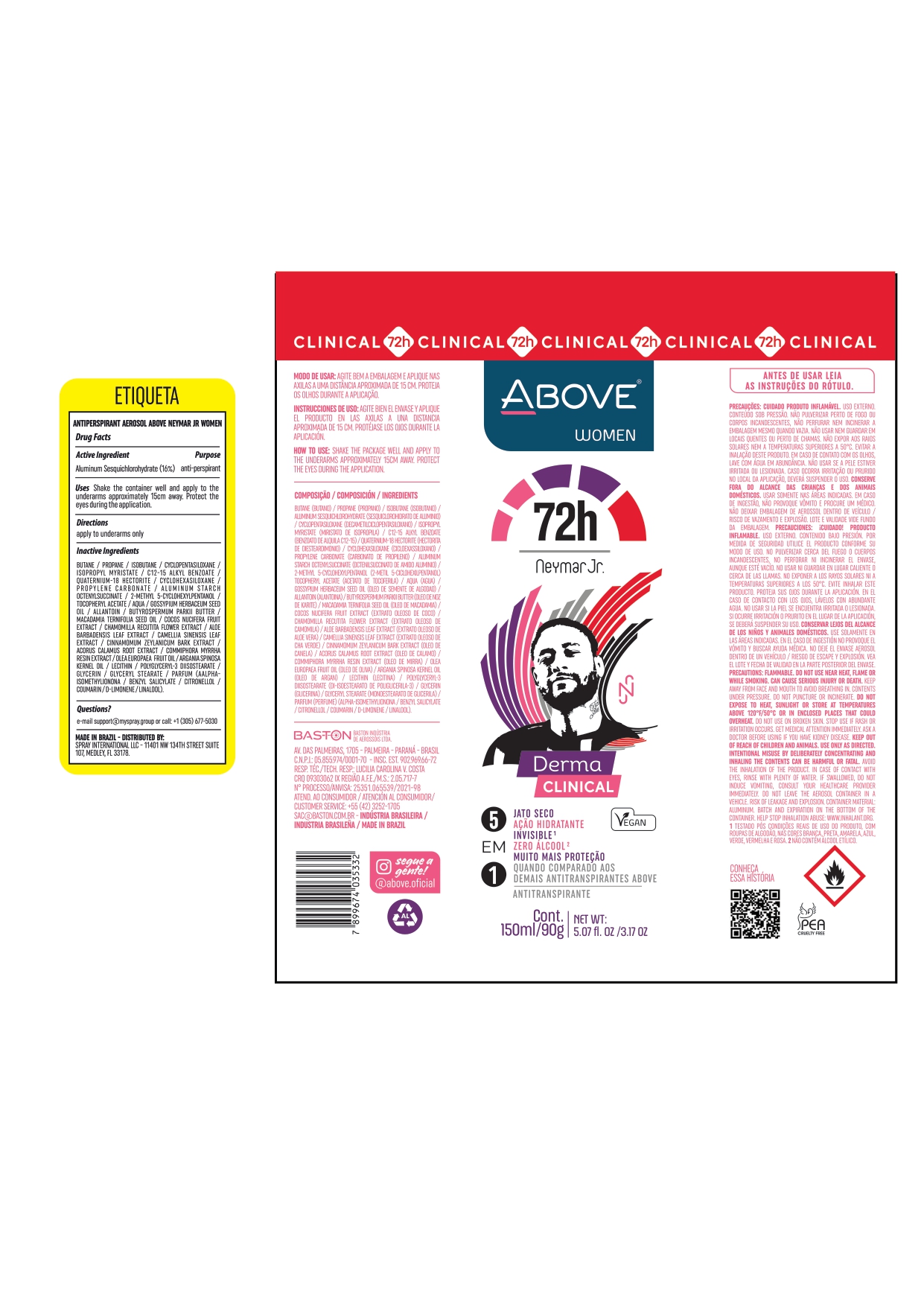 DRUG LABEL: ANTIPERSPIRANT ABOVE NEYMAR JR WOMEN
NDC: 73306-1130 | Form: AEROSOL
Manufacturer: BASTON INDUSTRIA DE AROSSOIS LTDA
Category: otc | Type: HUMAN OTC DRUG LABEL
Date: 20241226

ACTIVE INGREDIENTS: ALUMINUM SESQUICHLOROHYDRATE 16 g/100 g
INACTIVE INGREDIENTS: BUTANE

ANTIPERSPIRANT ABOVE NEYMAR JR WOMEN

ALUMINUM SESQUICHLOROHYDRATE

ALUMINUM SESQUICHLOROHYDRATE 16 %

deodorant antiperspirant

SHAKE WELL AND APPLY TO THE ARMPITS FROM A DISTANCE OF ABOUT 15 CM. PROTECT YOUR EYES DURING APPLICATION

APPLY TO UNDERARMS ONLY

INACTIVE INGREDIENT

BUTANE
PROPANE
ISOBUTANE
CYCLOPENTASILOXANE
ISOPROPYL MYRISTATE
C12-15 ALKYL BENZOATE
PARFUM
QUATERNIUM-18 HECTORITE
CYCLOHEXASILOXANE
PROPYLENE CARBONATE
ALUMINUM STARCH OCTENYLSUCCINATE
2-METHYL 5-CYCLOHEXYLPENTANOL
TOCOPHERYL ACETATE
AQUA
GOSSYPIUM HERBACEUM SEED OIL
ALLANTOIN
BUTYROSPERMUM PARKII BUTTER
MACADAMIA TERNIFOLIA SEED OIL
COCOS NUCIFERA FRUIT EXTRACT
CHAMOMILLA RECUTITA FLOWER EXTRACT
ALOE BARBADENSIS LEAF EXTRACT
CAMELLIA SINENSIS LEAF EXTRACT
CINNAMOMUM ZEYLANICUM BARK EXTRACT
ACORUS CALAMUS ROOT EXTRACT
COMMIPHORA MYRRHA RESIN EXTRACT
OLEA EUROPAEA FRUIT OIL
ARGANIA SPINOSA KERNEL OIL
LECITHIN
POLYGLYCERYL-3 DIISOSTEARATE
GLYCERIN
GLYCERYL STEARATE

QUESTIONS

E-MAIL : SAC@BASTON.COM.BR

FLAMMABLE PRODUCT. CONTENTS UNDER PRESSURE.

FLAMMABLE PRODUCT.
CONTENTS UNDER PRESSURE.